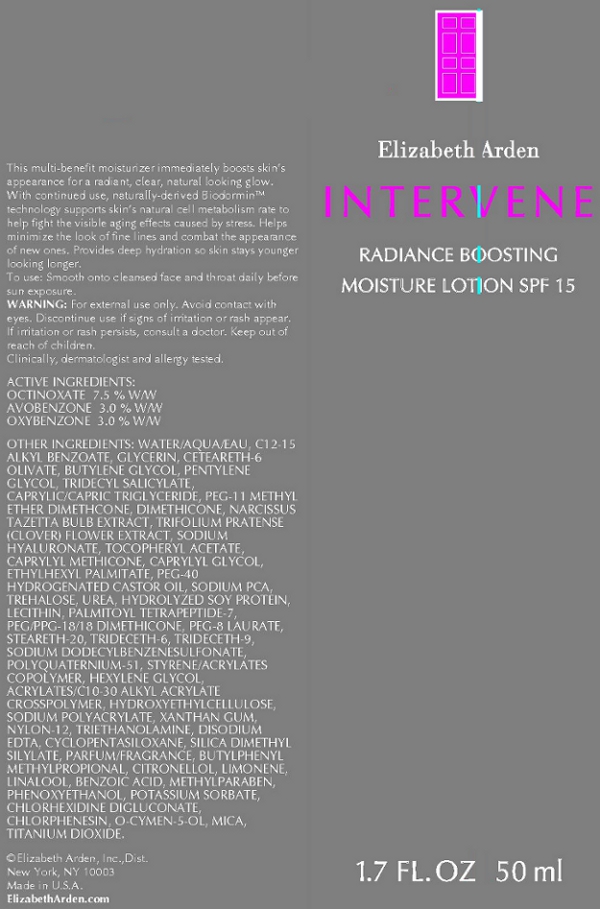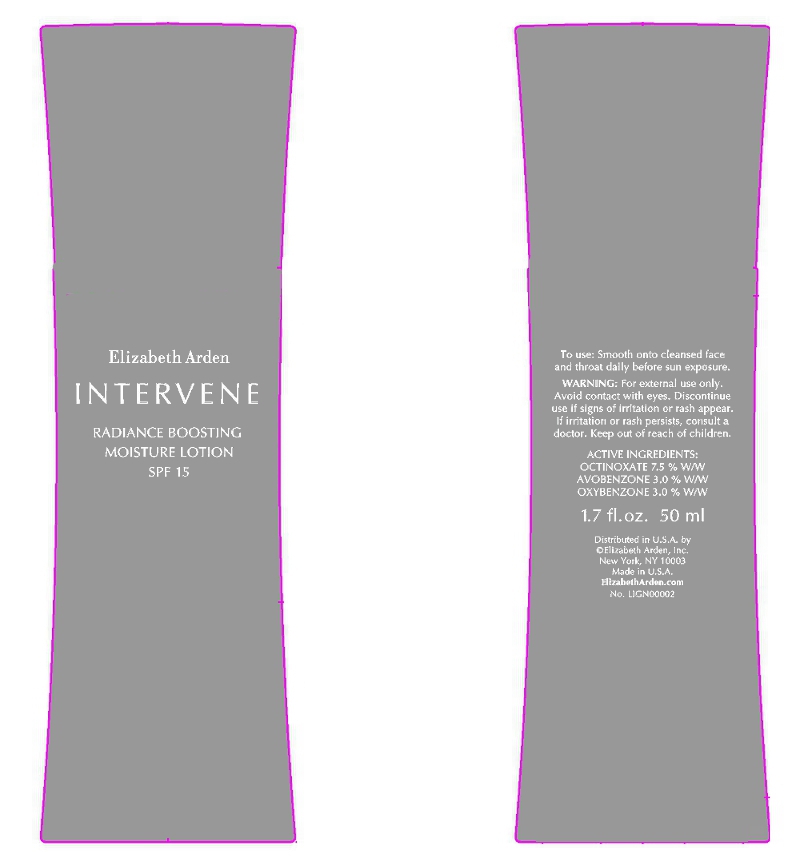 DRUG LABEL: Intervene Radiance Boosting Moisture SPF 15
NDC: 67938-0808 | Form: LOTION
Manufacturer: Elizabeth Arden, Inc
Category: otc | Type: HUMAN OTC DRUG LABEL
Date: 20110113

ACTIVE INGREDIENTS: OCTINOXATE 3.75 mL/50 mL; AVOBENZONE 1.5 mL/50 mL; OXYBENZONE 1.5 mL/50 mL
INACTIVE INGREDIENTS: WATER; ALKYL (C12-15) BENZOATE; GLYCERIN; PENTYLENE GLYCOL; MEDIUM-CHAIN TRIGLYCERIDES; DIMETHICONE; ETHYLHEXYL PALMITATE; PHENOXYETHANOL; TROLAMINE; SODIUM PYRROLIDONE CARBOXYLATE; UREA; MICA; POLYOXYL 40 HYDROGENATED CASTOR OIL; CYCLOMETHICONE 5; NARCISSUS TAZETTA BULB; TRIDECETH-6; PEG-8 LAURATE; O-CYMEN-5-OL; TREHALOSE; EDETATE DISODIUM; XANTHAN GUM; STEARETH-20; PROPYLENE GLYCOL; METHYLPARABEN; CAPRYLYL GLYCOL; SODIUM DODECYLBENZENESULFONATE; HYALURONATE SODIUM; CHLORPHENESIN; TRIFOLIUM PRATENSE FLOWER; STANNIC OXIDE; ALPHA-TOCOPHEROL; CHLORHEXIDINE GLUCONATE; POTASSIUM SORBATE; BENZOIC ACID; HEXYLENE GLYCOL; PALMITOYL TETRAPEPTIDE-7

BB0808

DESCRIPTION

This multi-benefit moisturizer immediately boosts skin's appearance for a radiant, clear, natural looking glow. With continued use, naturally-derived Biodormin technology supports skin's natural cell metabolism rate to help fight the visible aging effects caused by stress. Helps minimze the look of fine lines and combat the appearance of new ones. Provides deep hydration so skin stays younger looking longer. Clinically, dermatologist, and allergy tested.

INDICATIONS AND USAGE

To Use: Smooth on to cleansed face and throat daily before sun exposure.

WARNINGS

Warnings: For external use only. Avoid contact with eyes. Discontinue use if signs of irritation or rash appear. If irritation or rash persists, consult a doctor. Keep out of reach of children.

OTC - ACTIVE INGREDIENT

Active Ingredients: Octinoxate 7.5% w/w, Avobenzone 3.0% w/w, Oxybenzone 3.0% w/w.

INACTIVE INGREDIENT

Other Ingredients: Water/Aqua/Eau, Ethylhexyl Methoxycinnamite, C12-15 Alkyl Benzoate, Glycerin, Ceteareth-6 Olivate, Butylene Glycol, Benzophenone-3, Butyl Methoxydibenzoylmethane, Pentylene Glycol, Tridecyl Salicylate, Caprylice/Capric Triglyceride, PEG-11 Methyl Ehter Dimethcone, Dimethicone, Narcissus Tazetta Bulb Extract, Trifolium Pratense (Clover) Flower Extract, Sodium Hyaluronate, Tocopherol, Tocopheryl Acetate, Caprylyl Methicone, Caprylyl Glycol, Ethylhexyl Palmitate, PEG-40 Hydrogenated Castor Oil, Propylene Glycol, Sodium PCA, Trehalose, Urea, Hydrolyzed Soy Protein, Lecithin, Palmitoyl Tetrapeptide-7, PEG/PPG-18/18 Dimethicone, PEG-8 Laurate, Steareth-20, Trideceth-6, Trideceth-9, Sodium Dodecylbenzenesulfonate, Polyquaternium-51, Styrene/Acrylates Copolymer, Hexylene Glycol, Acrylates C10-30 Alkyl Acrylate Crosspolymer, Hydroxyethylcellulose, Sodium Polyacrylate, Xanthan Gum, Nylon-12, Triethanolamine, Disodium EDTA, Mica, Tin Oxide, Cyclopentasiloxane, Silica, Dimethyl Silylate, Parfum/Fragrance, Butylphenyl Methylpropional, Citronellol, Limonene, Linalool, Benzoic Acid, Methylparaben, Phenoxyethanol, Potassium Sorbate, Chlorhexidine Digluconate, Chlorphenesin, O-Cymen-5-ol, Titanium Dioxide (CI77891).

DOSAGE & ADMINISTRATION

Smooth on to face and throat.

OTC - KEEP OUT OF REACH OF CHILDREN

Keep out of reach of children.

OTC - PURPOSE

Provides SPF 15 sun protection.

OTC - WHEN USING

Avoid contact with eyes.